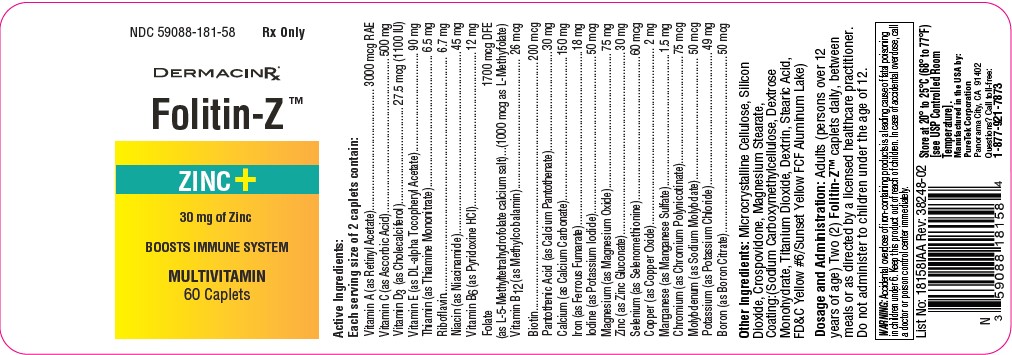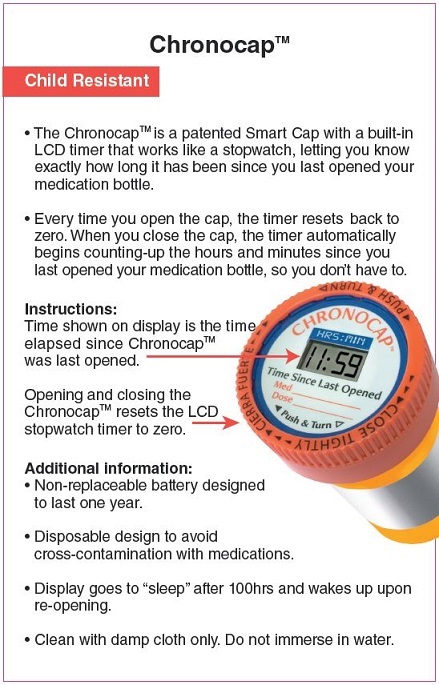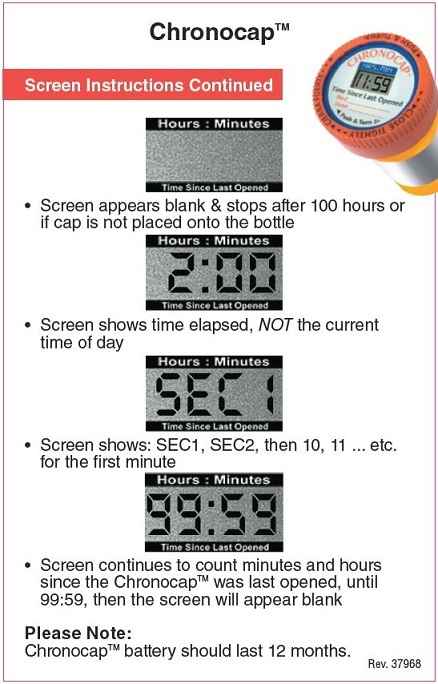 DRUG LABEL: Folitin-Z
NDC: 59088-181 | Form: TABLET
Manufacturer: PureTek Corporation
Category: prescription | Type: HUMAN PRESCRIPTION DRUG LABEL
Date: 20241202

ACTIVE INGREDIENTS: VITAMIN A ACETATE 1500 ug/1 1; ASCORBIC ACID 250 mg/1 1; CHOLECALCIFEROL 13.75 ug/1 1; .ALPHA.-TOCOPHEROL ACETATE, DL- 45 mg/1 1; THIAMINE MONONITRATE 3.25 mg/1 1; RIBOFLAVIN 3.35 mg/1 1; NIACINAMIDE 22.5 mg/1 1; PYRIDOXINE HYDROCHLORIDE 6 mg/1 1; FOLIC ACID 500 ug/1 1; CYANOCOBALAMIN 13 ug/1 1; BIOTIN 100 ug/1 1; PANTOTHENIC ACID 15 mg/1 1; CALCIUM CARBONATE 75 mg/1 1; FERROUS FUMARATE 9 mg/1 1; POTASSIUM IODIDE 25 ug/1 1; MAGNESIUM OXIDE 37.5 mg/1 1; ZINC OXIDE 15 mg/1 1; SELENIUM 30 ug/1 1; CUPROUS OXIDE 1 mg/1 1; MANGANESE SULFATE 0.75 mg/1 1; CHROMIUM NICOTINATE 37.5 ug/1 1; MOLYBDENUM 25 ug/1 1; POTASSIUM CHLORIDE 24.5 mg/1 1; BORON 25 ug/1 1
INACTIVE INGREDIENTS: MICROCRYSTALLINE CELLULOSE; CROSPOVIDONE; SILICON DIOXIDE; MAGNESIUM STEARATE; CARBOXYMETHYLCELLULOSE SODIUM, UNSPECIFIED; DEXTROSE MONOHYDRATE; TITANIUM DIOXIDE; ICODEXTRIN; STEARIC ACID; FD&C YELLOW NO. 6

Folitin-Z™

DESCRIPTION:

Full Prescribing Information:

Each Serving Size of 2 caplets contain:

Vitamin A (as Retinyl Acetate)................................................... 3000 mcg RAE
Vitamin C (as Ascorbic Acid)............................................................... 500 mg
Vitamin D (as Cholecalciferol).......................................... 3 27.5 mcg (1100 IU)
Vitamin E (as DL-alpha Tocopheryl Acetate)........................................... 90 mg
Thiamin (as Thiamine Mononitrate)....................................................... 6.5 mg
Riboflavin ............................................................................................. 6.7 mg
Niacin (as Niacinamide)......................................................................... 45 mg
Vitamin B6 (as Pyridoxine HCl)............................................................... 12 mg

Folate 1700 mcg DFE

(as L-5-Methyltetrahydrofolate calcium salt).........(1000 mcg as L-Methyfolate)

Vitamin B12 (as Methylcobalamin)....................................................... 26 mcg
Biotin ................................................................................................ 200 mcg
Pantothenic Acid (as Calcium Pantothenate)........................................... 30 mg
Calcium (as Calcium Carbonate)...........................................................150 mg
Iron (as Ferrous Fumarate)......................................................................18 mg
Iodine (as Potassium Iodide)................................................................50 mcg
Magnesium (as Magnesium Oxide)........................................................ 75 mg
Zinc (as Zinc Gluconate)......................................................................... 30 mg
Selenium (as Selenomethionine)...........................................................60 mcg
Copper (as Copper Oxide)....................................................................... 2 mg
Manganese (as Manganese Sulfate).......................................................1.5 mg
Chromium (as Chromium Polynicotinate)..............................................75 mcg
Molybdenum (as Sodium Molybdate)................................................... 50 mcg
Potassium (as Potassium Chloride)....................................................... 49 mg
Boron (as Boron Citrate)...................................................................... 50 mcg

Other Ingredients: Microcrystalline Cellulose, Silicon Dioxide, Crospovidone, Magnesium Stearate, Coating:(Sodium Carboxymethylcellulose, Dextrose Monohydrate, Titanium Dioxide, Dextrin, Purified Stearic Acid, FD&C Yellow #6/Sunset Yellow FCF Aluminum Lake).

INDICATIONS:

Folitin-ZTM is indicated for the treatment of iron deficiency anemia and folate deficiency as in extended convalescence, menorrhagia, pregnancy, puberty, excessive blood loss, and advanced age. Also for the treatment of the condition in which iron deficiency and vitamin C deficiency occurs together, along with a deficient intake or increased need for B-Complex vitamins in chronic and acute illness, as well as cases of metabolic stress, and in convalescence.

CONTRAINDICATIONS:

This product is contraindicated in patients with known hypersensitivity to any of its ingredients; also, all iron compounds are contraindicated in patients with hemosiderosis, hemochromatosis, or hemolytic anemias. Pernicious anemia is a contraindication, as folic acid may obscure its signs and symptoms.

WARNING:

Accidental overdose of iron-containing products is a leading cause of fatal poisoning in children under 6. Keep this product out of reach of children. In case of accidental overdose, call a doctor or poison control center immediately.
Administration of folic acid alone is improper therapy for pernicious anemia and other megaloblastic anemias in which vitamin B12 is deficient.

Precaution Section

Folic acid in doses above 0.1 mg daily may obscure pernicious anemia, in that hematologic remission can occur while neurological manifestations remain progressive.

There is a potential danger in administering folic acid to patients with undiagnosed anemia, since folic acid may obscure the diagnosis of pernicious anemia by alleviating the hematologic manifestations of the disease while allowing the neurologic complications to progress. This may result in severe nervous system damage before the correct diagnosis is made. Adequate doses of vitamin B12 may prevent, halt, or improve the neurologic changes caused by pernicious anemia.
The patient’s medical conditions and consumption of other drugs, herbs, and/or supplements should be considered.

For use on the order of a healthcare practitioner.
Call your doctor about side effects. To report side effects, call PureTek Corporation at
1-877-921-7873 or FDA at 1-800-FDA-1088 or www.fda.gov/medwatch.

Drug Interactions:

Folitin-ZTM is not recommended for and should not be given to patients receiving levodopa because the action of levodopa is antagonized by pyridoxine. There is a possibility of increased bleeding due to pyridoxine interaction with anticoagulants (e.g., Aspirin, Heparin, or Clopidogrel).

Adverse Reactions:

Folic Acid: Allergic sensitizations have been reported following both oral and parenteral administration of folic acid.
Ferrous Fumarate: Gastrointestinal disturbances (anorexia, nausea, diarrhea, constipation) occur occasionally, but are usually mild and may subside with continuation of therapy. Although the absorption of iron is best when taken between meals, giving Folitin-ZTM after meals may control occasional gastrointestinal disturbances. Folitin-ZTM is best absorbed when taken at bedtime. Adverse reactions have been reported with specific vitamins and minerals but generally at levels substantially higher than those contained herein. However, allergic and idiosyncratic reactions are possible at lower levels. Iron, even at the usually recommended levels, has been associated with gastrointestinal intolerance in some patients.

OVERDOSE:

Iron: Signs and Symptoms: Iron is toxic. Acute overdosage of iron may cause nausea and vomiting and, in severe cases, cardiovascular collapse and death. Other symptoms include pallor and cyanosis, melena, shock, drowsiness, and coma. The estimated overdose of orally ingested iron is 300 mg/kg body weight. When overdoses are ingested by children, severe reactions, including fatalities, have resulted. Folitin-ZTM should be stored beyond the reach of children to prevent against accidental iron poisoning. Keep this and all other drugs out of reach of children.

Treatment:

For specific therapy, exchange transfusion and chelating agents should be used. For general management, perform gastric lavage with sodium bicarbonate solution or milk. Administer intravenous fluids and electrolytes and use oxygen.

DOSAGE AND ADMINISTRATION:

Adults (persons over 12 years of age) Two (2) Folitin-ZTM caplet daily, between meals or as directed by a physician. Do not administer to children under the age of 12.

HOW SUPPLIED:

Folitin-ZTM are yellow with slightly brown speckled, coated caplets. Bottles contain 60 caplets – NDC 59088-181-58. Dispense in a tight, light-resistant container as defined in the USP/NF with a child-resistant closure.

STORAGE:

Do not use if bottle seal is broken.
KEEP THIS AND ALL MEDICATIONS OUT OF THE REACH OF CHILDREN.
Store at controlled room temperature 20o to 25oC (68o to 77oF). [See USP].
Protect from light and moisture and avoid excessive heat.
To report a serious adverse event or to obtain product information, contact
1-877-921-7873.

Folitin-ZTM

Manufactured in the USA by:
PureTek Corporation
Panorama City, CA 91402
Questions? Call toll-free:
1-877-921-7873